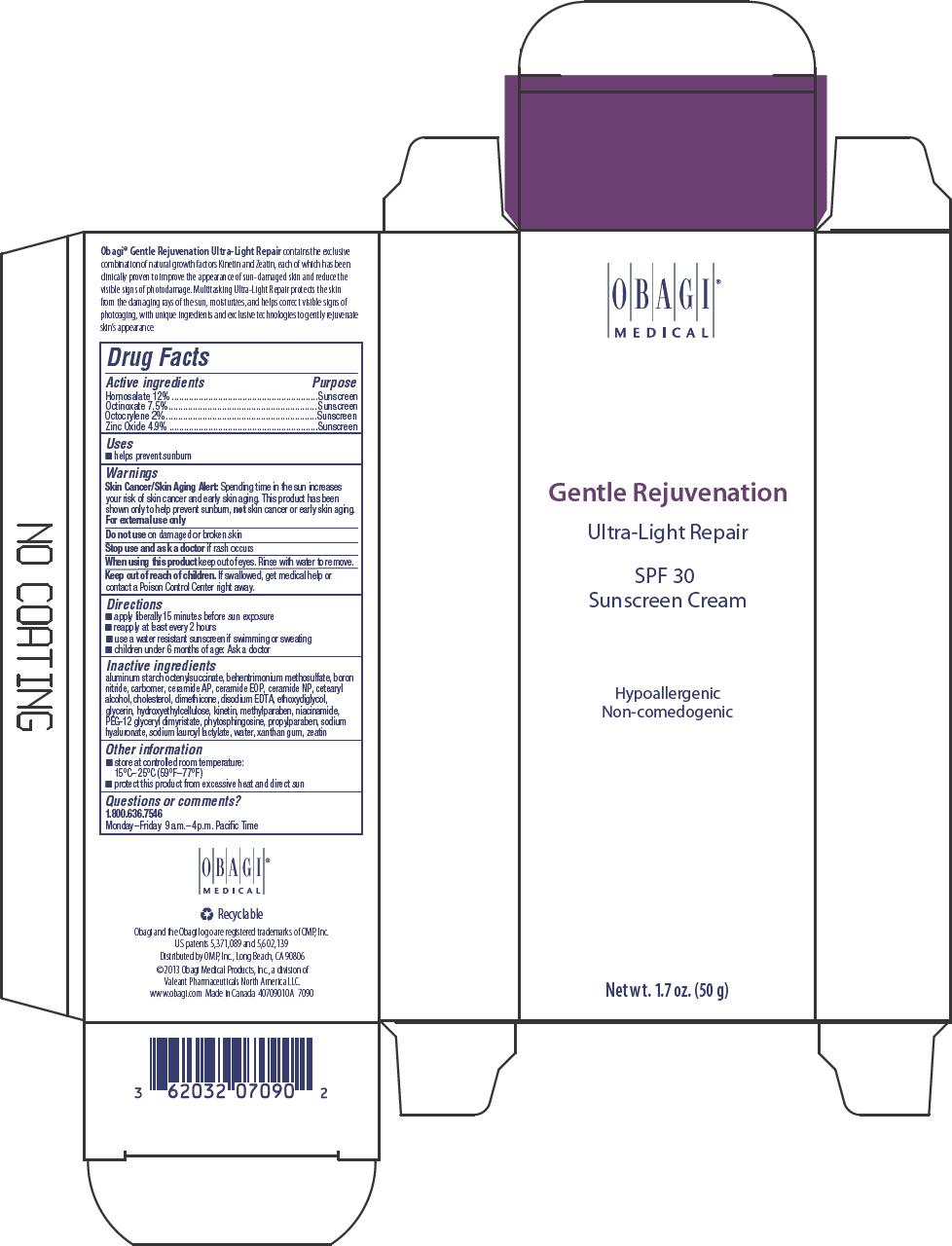 DRUG LABEL: GENTLE REJUVENATION ULTRA LIGHT REPAIR SPF 30
NDC: 62032-131 | Form: CREAM
Manufacturer: Obagi Medical Products, Inc., a division of Valeant Pharmaceuticals North America LLC.
Category: otc | Type: HUMAN OTC DRUG LABEL
Date: 20131015

ACTIVE INGREDIENTS: HOMOSALATE 120 mg/1 g; OCTINOXATE 75 mg/1 g; OCTOCRYLENE 20 mg/1 g; ZINC OXIDE 49 mg/1 g
INACTIVE INGREDIENTS: ALUMINUM STARCH OCTENYLSUCCINATE; BEHENTRIMONIUM METHOSULFATE; BORON NITRIDE; CARBOMER HOMOPOLYMER TYPE B (ALLYL SUCROSE CROSSLINKED); CERAMIDE 6 II; CERAMIDE 1; CERAMIDE 3; CETOSTEARYL ALCOHOL; CHOLESTEROL; DIMETHICONE 100; EDETATE DISODIUM; DIETHYLENE GLYCOL MONOETHYL ETHER; GLYCERIN; KINETIN; METHYLPARABEN; NIACINAMIDE; PEG-12 GLYCERYL DIMYRISTATE; PHYTOSPHINGOSINE; PROPYLPARABEN; HYALURONATE SODIUM; SODIUM LAUROYL LACTYLATE; WATER; XANTHAN GUM; ZEATIN

GENTLE REJUVENATION ULTRA LIGHT REPAIR SPF 30
SUNSCREEN CREAM

Drug Facts

ACTIVE INGREDIENT

Active ingredients | Purpose
Homosalate 12% | Sunscreen
Octinoxate 7.5% | Sunscreen
Octocrylene 2% | Sunscreen
Zinc Oxide 4.9% | Sunscreen

Uses

- helps prevent sunburn

Warnings

Skin Cancer/Skin Aging Alert

Spending time in the sun increases your risk of skin cancer and early skin aging. This product has been shown only to help prevent sunburn, not skin cancer or early skin aging.

For external use only

Do not use on damaged or broken skin

Stop use and ask a doctor if rash occurs

When using this product keep out of eyes. Rinse with water to remove.

Keep out of reach of children. If swallowed, get medical help or contact a Poison Control Center right away.

Directions

- apply liberally 15 minutes before sun exposure
- reapply at least every 2 hours
- use a water resistant sunscreen if swimming or sweating
- children under 6 months of age: Ask a doctor

Inactive ingredients

aluminum starch octenylsuccinate, behentrimonium methosulfate, boron nitride, carbomer, ceramide AP, ceramide EOP, ceramide NP, cetearyl alcohol, cholesterol, dimethicone, disodium EDTA, ethoxydiglycol, glycerin, hydroxyethylcellulose, kinetin, methylparaben, niacinamide, PEG-12 glyceryl dimyristate, phytosphingosine, propylparaben, sodium hyaluronate, sodium lauroyl lactylate, water, xanthan gum, zeatin

Other information

- store at controlled room temperature:
  15°C–25°C (59°F–77°F)
- protect this product from excessive heat and direct sun

Questions or comments?

1.800.636.7546
Monday–Friday 9 a.m.–4 p.m. Pacific Time

Distributed by OMP, Inc., Long Beach, CA 90806

PRINCIPAL DISPLAY PANEL - 50 g Tube Carton

OBAGI®
MEDICAL

Gentle Rejuvenation
Ultra-Light Repair
SPF 30
Sunscreen Cream

Hypoallergenic
Non-comedogenic

Net wt. 1.7 oz. (50 g)